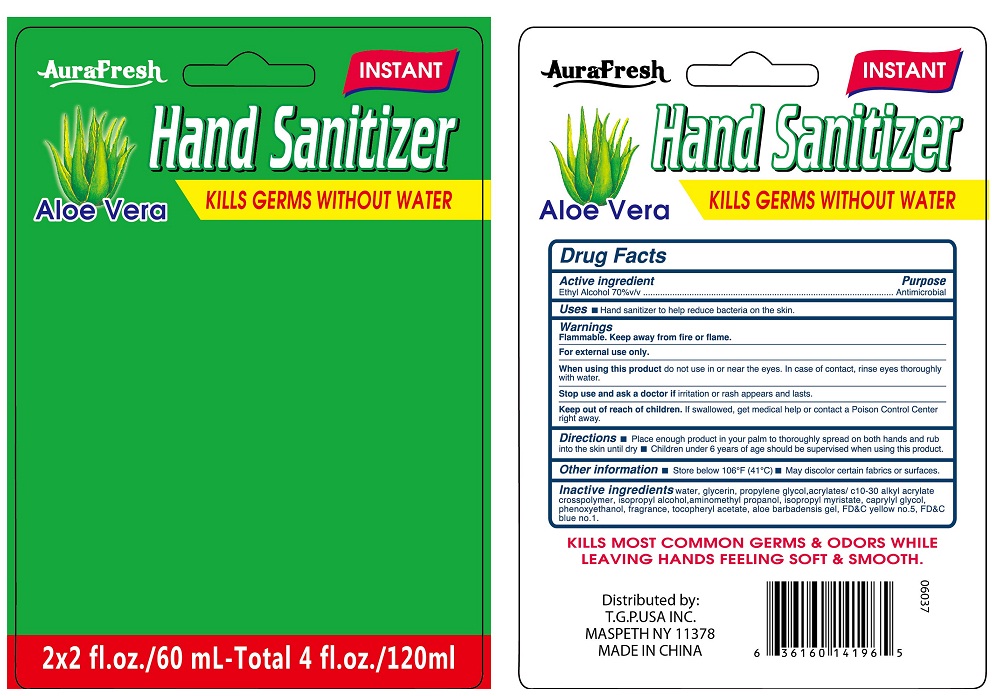 DRUG LABEL: aurafresh instant hand sanitizer
NDC: 40104-283 | Form: GEL
Manufacturer: Ningbo Pulisi Daily Chemical Products Co., Ltd.
Category: otc | Type: HUMAN OTC DRUG LABEL
Date: 20170811

ACTIVE INGREDIENTS: alcohol 70 mL/100 mL
INACTIVE INGREDIENTS: WATER; PROPYLENE GLYCOL; ALOE VERA LEAF; CARBOMER 934; GLYCERIN; .ALPHA.-TOCOPHEROL ACETATE, D-; TROLAMINE; CARBOMER COPOLYMER TYPE A; ISOPROPYL ALCOHOL; AMINOMETHYLPROPANOL; CAPRYLYL GLYCOL; PHENOXYETHANOL; FD&C BLUE NO. 1; FD&C YELLOW NO. 5

Drug facts

Active ingredient Purpose

Ethyl Alcohol 70% ... Antiseptic

PURPOSE

Hand sanitizer to help decrease bacteria on the skin.

KEEP OUT OF REACH OF CHILDREN

If swallowed, get medical help or contact local poison control center right away.

Children under 6 years of age should be supervised when using this products.

when using this product, do not use in or near the eyes. In case of contact, rinse eyes thoroughly with water.

WARNINGS

For external use only.
Flammable. Keep away from hear or flame.

Stop using and ask a doctor, if irritation or rash appears and lasts.

DOSAGE AND ADMINISTRATION

place enough product in your palm and thoroughly spread on both hands, and rub into the skin until dry.

other information: store below 106 Degrees Fahrenheit (41 Degrees Centigrade); may discolor certain fabrics or surface.

INACTIVE INGREDIENT

Water, Carbomer, Glycerin, Propylene Glycol, acrylates/c10-30 alkyl acrylate crosspolymer, isopropyl alcohol, aminoethyl propanol, isopropyl myristate, caprylyl glycol, phenoxyenthanol, Triethanolamine, Aloe Barbadensis Leaf Juice, Tocopheryl Acetate, Fragrance, blue 1, yellow 5